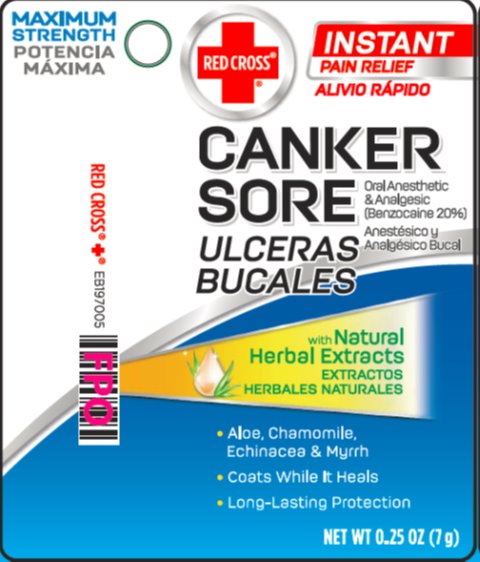 DRUG LABEL: Red Cross Canker Sore
NDC: 10742-8915 | Form: OINTMENT
Manufacturer: The Mentholatum Company
Category: otc | Type: HUMAN OTC DRUG LABEL
Date: 20241217

ACTIVE INGREDIENTS: BENZOCAINE 200 mg/1 g
INACTIVE INGREDIENTS: ALOE VERA LEAF; BUTYLATED HYDROXYTOLUENE; CARBOMER HOMOPOLYMER TYPE B (ALLYL PENTAERYTHRITOL CROSSLINKED); CETYLPYRIDINIUM CHLORIDE; CHAMOMILE; COCONUT OIL; MYRRH; ECHINACEA PURPUREA; GLYCERYL 1-STEARATE; MENTHOL, UNSPECIFIED FORM; MINERAL OIL; SILICA DIMETHYL SILYLATE; .ALPHA.-TOCOPHEROL; PETROLATUM

Drug Facts - Red Cross Canker Sore

Active ingredient

Benzocaine 20%

Purpose

Oral anesthetic/analgesic

Uses

temporarily relieves pain and minor irritation of the mouth and gums due to ▪ canker sores ▪ minor dental procedures ▪ braces ▪ dentures

Warnings

Methemoglobinemia warning: Use of this product may cause methemoglobinemia, a serious condition that must be treated promptly because it reduces the amount of oxygen carried in blood. This can occur even if you have used this product before. Stop use and seek immediate medical attention if you or a child in your care develops: ▪ pale, gray, or blue colored skin (cyanosis) ▪ headache ▪ rapid heart rate ▪ shortness of breath ▪ dizziness or lightheadedness ▪ fatigue or lack of energy

Allergy alert: do not use this product if you have a history of allergy to local anesthetics such as procaine, butacaine, benzocaine or other “caine” anesthetics

Do Not Use

- for teething
- in children under 2 years of age

When using this product

- do not use for more than 7 days unless directed by a dentist or doctor
- do not exceed recommended dosage

Stop use and ask a doctor if

- sore mouth symptoms last more than 7 days
- irritation, pain, or redness persists or worsens
- swelling, rash, or fever develops

Keep Out of Reach of Children

If more than used for pain is accidentally swallowed, get medical help or contact a Poison Control Center right away.

Directions

- snip off tip of tube
- apply to affected area; carefully coat with a protective layer
- supervise children using this product
- adults and children 2 years and over: use up to 4 times daily or as directed by a doctor
- children under 2 years: do not use

Inactive Ingredients

aloe barbadensis leaf extract, butylated hydroxytoluene, carbomer hompolymer, cetylpyridinium chloride, chamomilla recutita (matricaria) flower extract, cocos nucifera (coconut) oil, commiphora myrrha resin, dimethicone, echinacea purpurea extract, flavor, glyceryl stearate, menthol, mineral oil, silica dimethicone silylate, vitamin E, white petrolatum